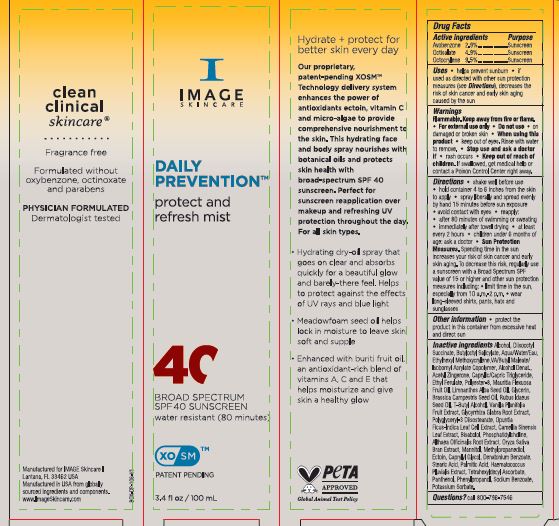 DRUG LABEL: Daily Prevention Protect and Refresh Mist SPF 40
NDC: 62742-4257 | Form: SPRAY
Manufacturer: Allure Labs
Category: otc | Type: HUMAN OTC DRUG LABEL
Date: 20240321

ACTIVE INGREDIENTS: OCTOCRYLENE 9.5 g/100 g; AVOBENZONE 2.9 g/100 g; OCTISALATE 4.9 g/100 g
INACTIVE INGREDIENTS: OPUNTIA FICUS-INDICA LEAF; GREEN TEA LEAF; DIISOBUTYL SUCCINATE; ISOBORNYL ACRYLATE; ACETYL ZINGERONE; STEARIC ACID; MEDIUM-CHAIN TRIGLYCERIDES; ETHYL FERULATE; RUBUS IDAEUS SEED; TETRAHEXYLDECYL ASCORBATE; PANTHENOL; POTASSIUM SORBATE; GLYCYRRHIZA GLABRA; LEVOMENOL; ALTHAEA OFFICINALIS ROOT; METHYLPROPANEDIOL; ECTOINE; DENATONIUM BENZOATE; HAEMATOCOCCUS PLUVIALIS; VANILLA BEAN; RICE BRAN; CAPRYLYL GLYCOL; PALMITIC ACID; SODIUM BENZOATE; WATER; ETHYLHEXYL METHOXYCRYLENE; DIBUTYL MALEATE; MAURITIA FLEXUOSA FRUIT OIL; MEADOWFOAM SEED OIL; GLYCERIN; BRASSICA RAPA SUBSP. RAPA SEED; TERT-BUTYL ALCOHOL; ALCOHOL; BUTYLOCTYL SALICYLATE; POLYESTER-8 (1400 MW, CYANODIPHENYLPROPENOYL CAPPED); POLYGLYCERYL-3 DIISOSTEARATE; PHENYLPROPANOL; PHOSPHATIDYLCHOLINE TRANSLOCATOR ABCB4; MANNITOL

Drug Facts

Active ingredients

Avobenzone 2.9%

Octisalate 4.9%

Octocrylene 9.5%

Purpose: Sunscreen

INDICATIONS AND USAGE

Uses • helps prevent sunburn • if used as directed with other sun protection measures (see Directions), decreases the risk of skin cancer and early skin aging caused by the sun.

WARNINGS

Warnings: Flammable. Keep away from fire or flame. • For external use only

Do not use • on damaged or broken skin

When using this product • keep out of eyes. Rinse with water to remove.

Stop use and ask a doctor if • rash occurs

Keep out of reach of children. if swallowed, get medical help or contact a Poison Control Center right away.

DOSAGE AND ADMINISTRATION

Directions • shake well before use • hold container 4 to 6 inches from the skin to apply • spray liberally and spread evenly by hand 15 minutes before sun exposure • avoid contact with eyes • reapply: • after 80 minutes of swimming or sweating • immediately after towel drying • at least every 2 hours • children under 6 months of age: ask a doctor • Sun Protection Measures. Spending time in the sun increases your risk of skin cancer and early skin aging. To decrease this risk, regularly use a sunscreen with a Broad Spectrum SPF value of 15 or higher and other sun protection measures including: • limit time in the sun, especially from 10 a.m.-2 p.m. • wear long-sleeved shirts, pants, hats and sunglasses

Other information • protect the product in this container from excessive heat and direct sun.

INACTIVE INGREDIENT

Inactive ingredients: Alcohol, Diisooctyl Succinate, Butyloctyl Salicylate, Aqua/water/Eau, Ethylhexyl Methoxycrylene, VA/Butyl Maleate/ Isobornyl Acrylate Copolymer, Alcohol Denat., Acetyl Zingerone, Caprylie/Capric Triglyceride, Ethyl Ferulate, Polyester-8, Mauritia Flexuosa Fruit Oil, Limnanthes Alba Seed Oil, Glycerin, Brassica Campestris Seed Oil, Rubus Idaeus Seed Oil, T-Butyl Alcohol, Vanilla Planifolia Fruit Extract, Glycyrrhiza Glabra Root Extract, Polyglyceryl-3 Diisostearate, Opuntia Ficus-Indica Leaf Cell Extract, Camellia Sinensis Leaf Extract, Bisabolol, Phosphatidylcholine, Althaea Officinalis Root Extract, Oryza Sativa Bran Extract, Mannitol, Methylpropanediol, Ectoin, Caprylyl Glycol, Denatonium Benzoate, Stearic Acid, Palmitic Acid, Haematococcus Pluvialis Extract, Tetrahexyldecyl Ascorbate, Panthenol, Phenylpropanol, Sodium Benzoate, Potassium Sorbate.